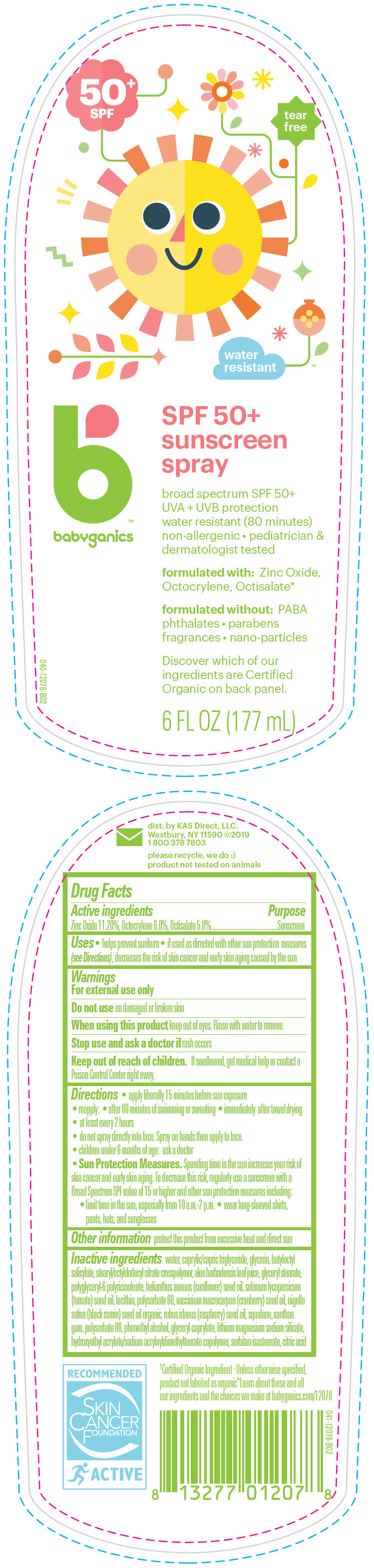 DRUG LABEL: BABYGANICS SPF 50 Plus SUNSCREEN
NDC: 59062-0120 | Form: SPRAY
Manufacturer: KAS Direct LLC dba Babyganics
Category: otc | Type: HUMAN OTC DRUG LABEL
Date: 20241220

ACTIVE INGREDIENTS: ZINC OXIDE 112 mg/1 mL; OCTISALATE 50 mg/1 mL; OCTOCRYLENE 60 mg/1 mL
INACTIVE INGREDIENTS: WATER; MEDIUM-CHAIN TRIGLYCERIDES; GLYCERIN; BUTYLOCTYL SALICYLATE; GLYCERYL MONOSTEARATE; POLYSORBATE 80; PHENYLETHYL ALCOHOL; GLYCERYL MONOCAPRYLATE; LAPONITE; XANTHAN GUM; HYDROXYETHYL ACRYLATE/SODIUM ACRYLOYLDIMETHYL TAURATE COPOLYMER (100000 MPA.S AT 1.5%); CITRIC ACID MONOHYDRATE; SQUALANE; TOMATO SEED OIL; SUNFLOWER OIL; SOYBEAN LECITHIN; POLYSORBATE 60; ALOE VERA LEAF; CRANBERRY SEED OIL; RASPBERRY SEED OIL; NIGELLA SATIVA SEED OIL; SORBITAN ISOSTEARATE

BABYGANICS SPF 50+ SUNSCREEN SPRAY

Drug Facts

Active ingredients

Zinc Oxide 11.20%, Octocrylene 6.0%, Octisalate 5.0%

Purpose

Sunscreen

Uses

- helps prevent sunburn
- if used as directed with other sun protection measures (see Directions), decreases the risk of skin cancer and early skin aging caused by the sun

Warnings

For external use only

Do not use on damaged or broken skin

When using this product keep out of eyes. Rinse with water to remove.

Stop use and ask a doctor if rash occurs

Keep out of reach of children. If swallowed, get medical help or contact a Poison Control Center right away.

Directions

- apply liberally 15 minutes before sun exposure
- reapply:
  - after 80 minutes of swimming or sweating
  - immediately after towel drying
  - at least every 2 hours
- do not spray directly into face. Spray on hands then apply to face.
- children under 6 months of age: ask a doctor
- Sun Protection Measures. Spending time in the sun increases your risk of skin cancer and early skin aging. To decrease this risk, regularly use a sunscreen with a Broad Spectrum SPF value of 15 or higher and other sun protection measures including:
  - limit time in the sun, especially from 10 a.m.-2 p.m.
  - wear long-sleeved shirts, pants, hats, and sunglasses

Other information

protect this product from excessive heat and direct sun

Inactive ingredients

water, caprylic/capric triglyceride, glycerin, butyloctyl salicylate, stearyl/octyldodecyl citrate crosspolymer, aloe barbadensis leaf juice, glyceryl stearate, polyglyceryl-6 polyricinoleate, helianthus annuus (sunflower) seed oil, solanum lycopersicum (tomato) seed oil, lecithin, polysorbate 60, vaccinium macrocarpon (cranberry) seed oil, nigella sativa (black cumin) seed oil organic, rubus idaeus (raspberry) seed oil, squalane, xanthan gum, polysorbate 80, phenethyl alcohol, glyceryl caprylate, lithium magnesium sodium silicate, hydroxyethyl acrylate/sodium acryloyldimethyltaurate copolymer, sorbitan isostearate, citric acid

dist. by KAS Direct, LLC.
Westbury, NY 11590

PRINCIPAL DISPLAY PANEL - 177 mL Bottle Label

50^+
SPF

tear
free

water
resistant

babyganics

SPF 50+
sunscreen
spray

broad spectrum SPF 50+
UVA + UVB protection
water resistant (80 minutes)
non-allergenic • pediatrician &
dermatologist tested

formulated with: Zinc Oxide,
Octocrylene, Octisalate*

formulated without: PABA
phthalates • parabens
fragrances • nano-particles

Discover which of our
ingredients are Certified
Organic on back panel.

6 FL OZ (177 mL)

040-12078-B02